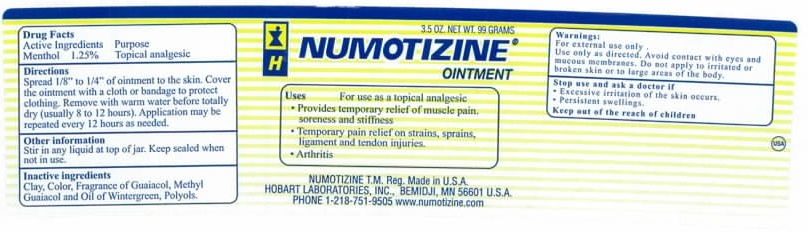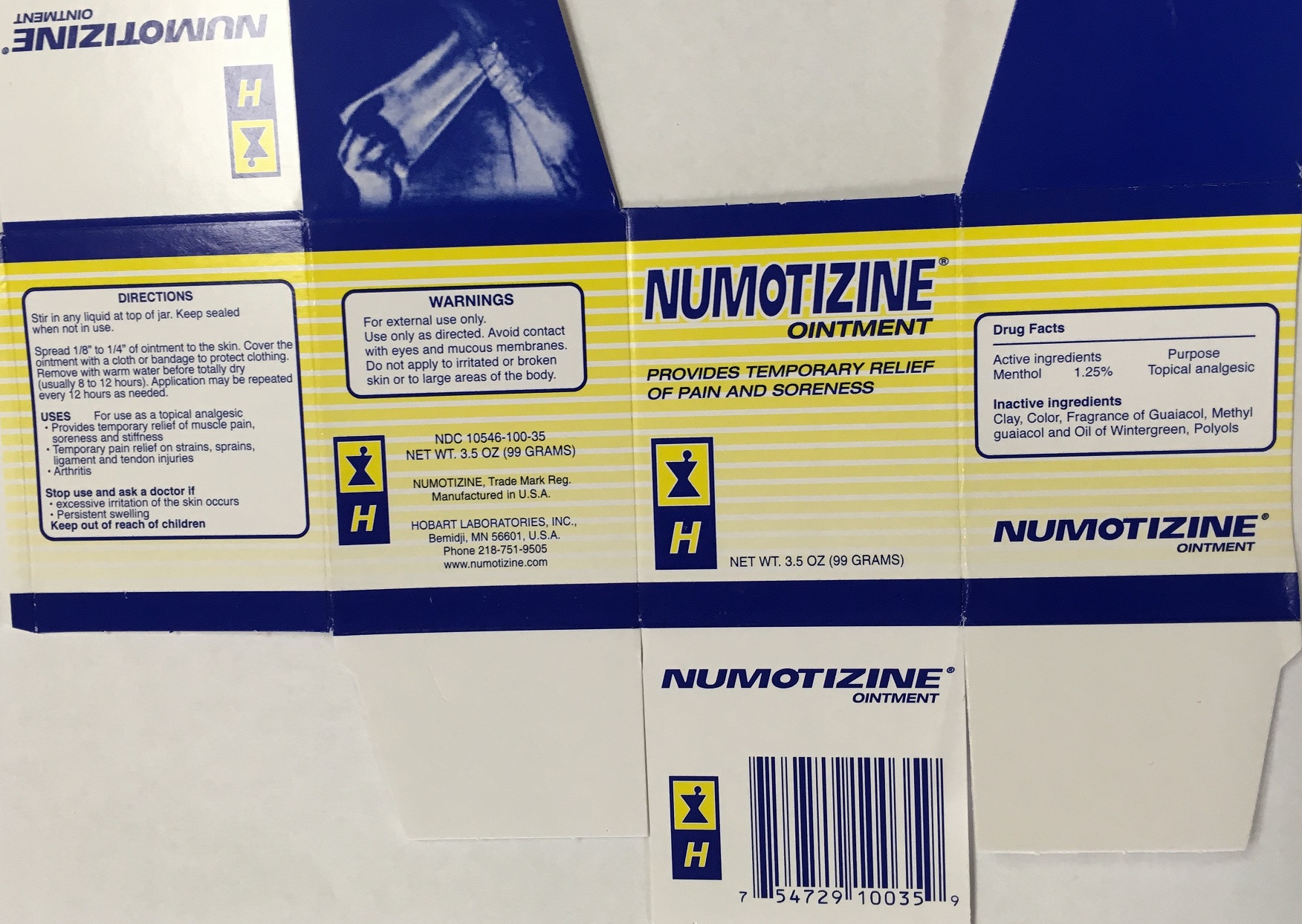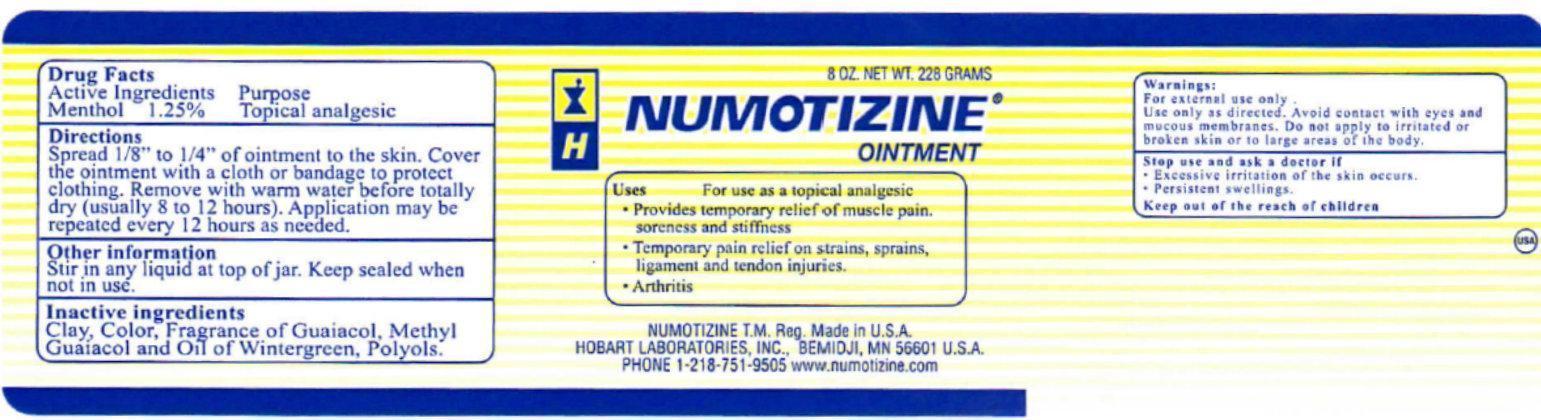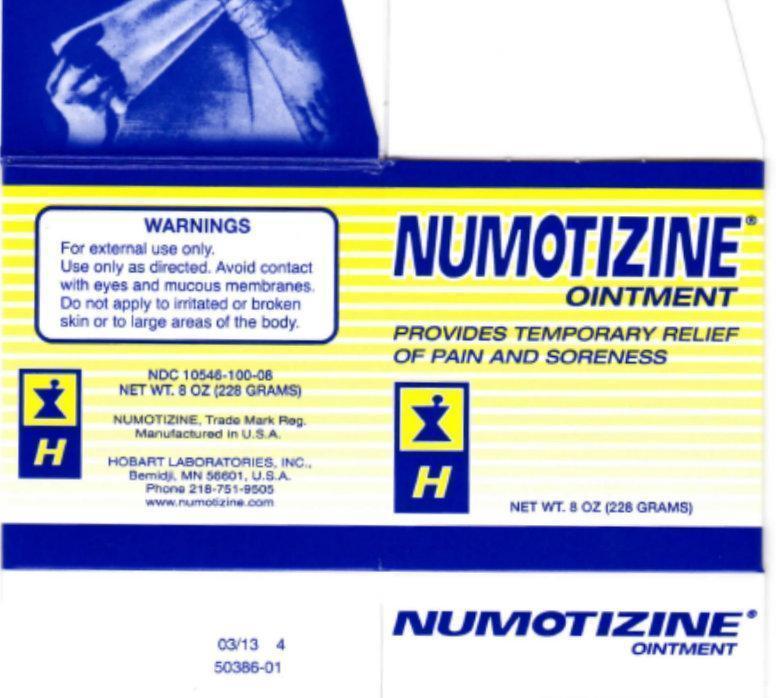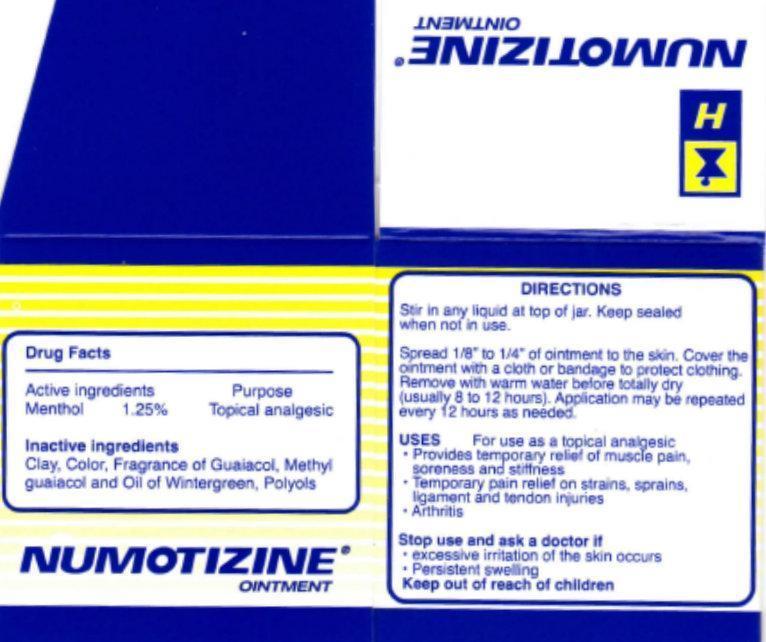 DRUG LABEL: NUMOTIZINE
NDC: 10546-100 | Form: OINTMENT
Manufacturer: Hobart Laboratories, Inc.
Category: otc | Type: HUMAN OTC DRUG LABEL
Date: 20231020

ACTIVE INGREDIENTS: MENTHOL 1.25 g/100 g
INACTIVE INGREDIENTS: KAOLIN; GUAIACOL; CREOSOL; METHYL SALICYLATE; PROPYLENE GLYCOL

NUMOTIZINE OINTMENT

Active Ingredients

Menthol 1.25%

Purpose

Topical Analgesic

Inactive ingredients

Clay, Color, Fragrance of Guaiacol, Methyl Guaiacol and Oil of Wintergreen, Polyols.

Directions

Stir in any liquid at top of jar. Keep sealed when not in use.

Spread 1/8" to 1/4" of ointment to the skin. Cover the ointment with a cloth or bandage to protect clothing. Remove with warm water before totally dry (usually 8 to 12 hours). Application may be repeated every 12 hours as needed.

Uses

For use as a topical analgesic

- Provides temporary relief of muscle pain, soreness and stiffness
- Temporary pain relief on strains, sprains, ligament and tendon injuries
- Arthritis

Stop use and ask a doctor if

- Excessive irritation of the skin occurs.
- Persistent swellings.

Warnings:

For external use only.

Use only as directed. Avoid contact with eyes and mucous memebranes.

Do not apply to irritated or broken skin or to large areas of the body.